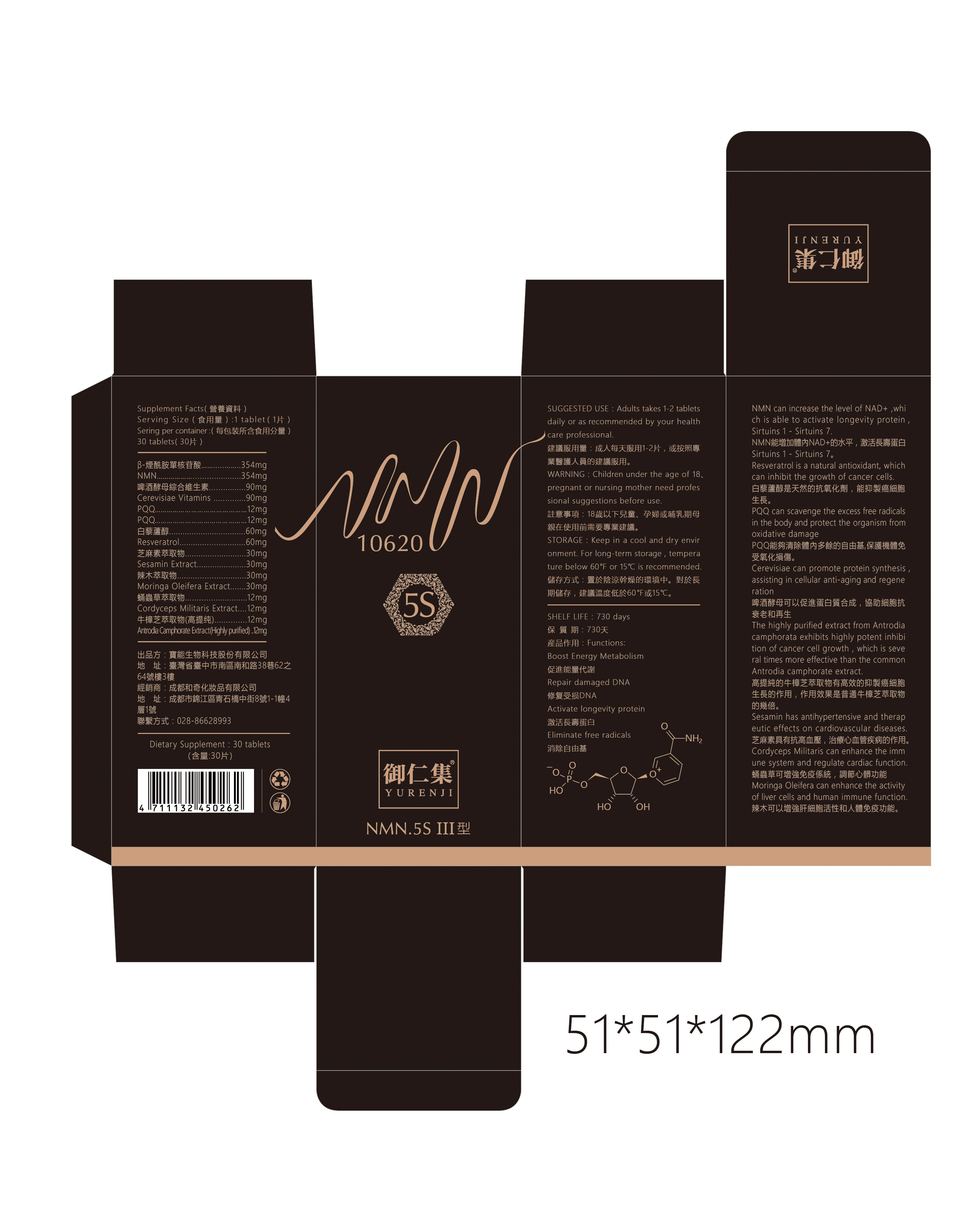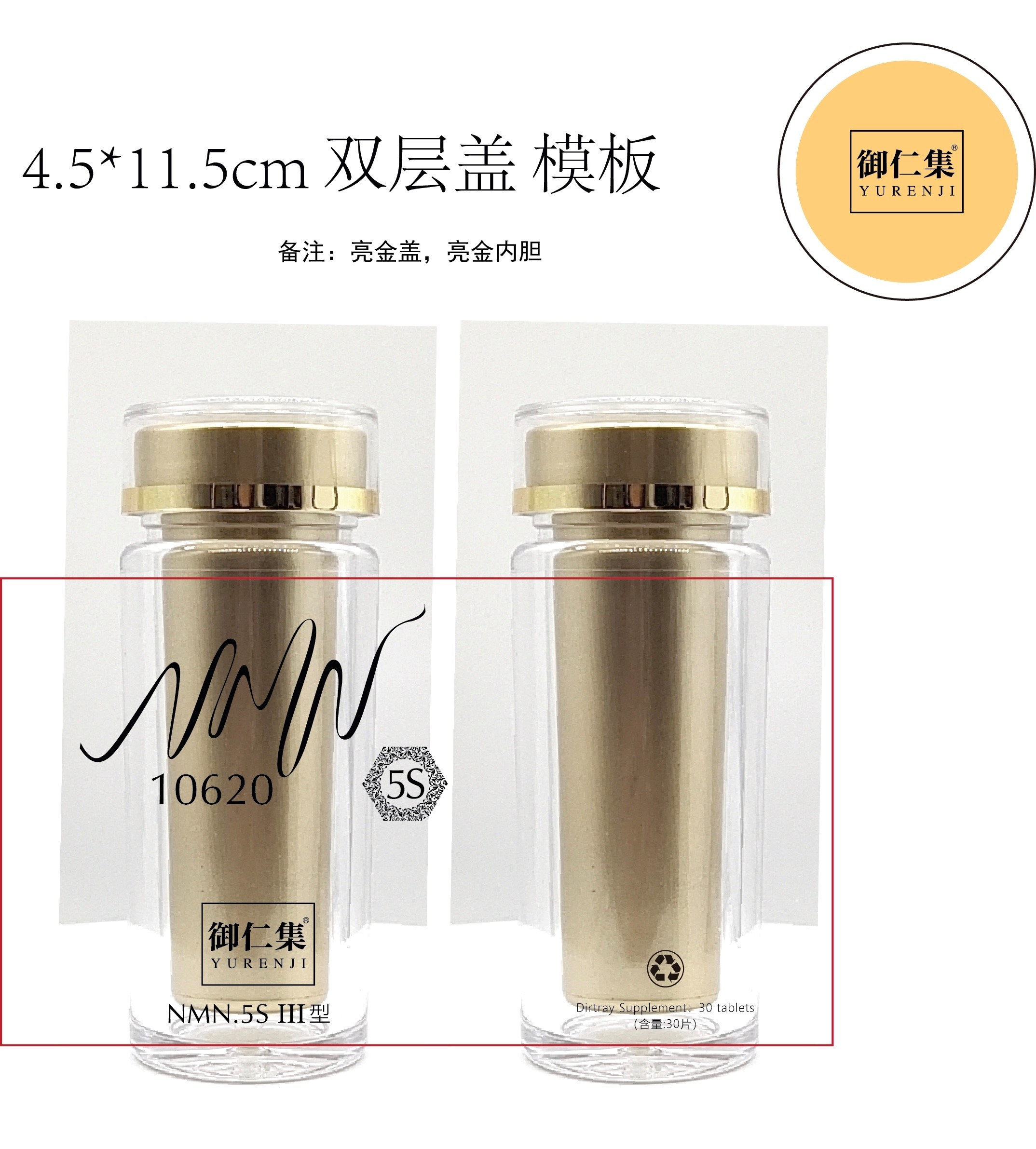 DRUG LABEL: NMN.5S
NDC: 81668-001 | Form: TABLET
Manufacturer: Chengdu Heqi Cosmetics Co., Ltd
Category: otc | Type: HUMAN OTC DRUG LABEL
Date: 20210305

ACTIVE INGREDIENTS: NICOTINAMIDE MONONUCLEOTIDE 354 mg/1 1; RESVERATROL 60 mg/1 1
INACTIVE INGREDIENTS: CORDYCEPS MILITARIS WHOLE; TAIWANOFUNGUS CAMPHORATUS WHOLE

ACTIVE INGREDIENT

RESVERATROL 10%

NICOTINAMIDE RIBOTIDE 50%

KEEP OUT OF REACH OF CHILDREN

PURPOSE

NMN can increase the level of NAD+ ,which is able to activate longevity protein ,Sirtuins 1 - Sirtuins 7.

INACTIVE INGREDIENT

CORDYCEPS MILITARIS WHOLE

TAIWANOFUNGUS CAMPHORATUS WHOLE

INDICATIONS AND USAGE

Boost Energy Metabolism

Repair damaged DNA

Activate longevity protein

Eliminate free radicals

SUGGESTED USE

Adults takes 1-2 tablets daily or as recommended by your health care professional.

WARNINGS

Children under the age of 18、pregnant or nursing mother need professional suggestions before use